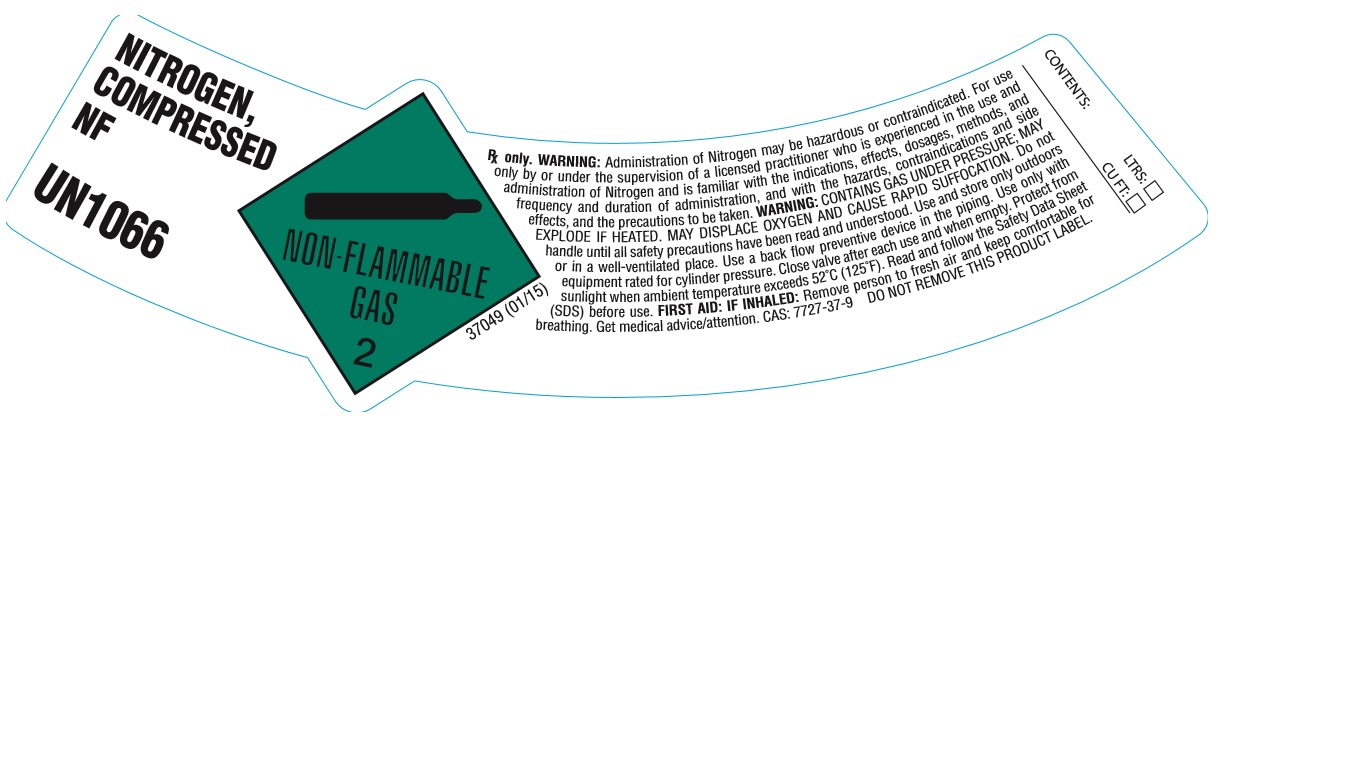 DRUG LABEL: Nitrogen
NDC: 21220-020 | Form: GAS
Manufacturer: General Air Service & Supply Co.
Category: animal | Type: PRESCRIPTION ANIMAL DRUG LABEL
Date: 20251126

ACTIVE INGREDIENTS: NITROGEN 999 mL/1 L

Nitrogen

PACKAGE LABEL

NITROGEN, COMPRESSED NF UN1066
NON-FLAMMABLE GAS 2
37049 (01/15)
Rx only. WARNING: Administration of Nitrogen may be hazardous or contraindicated. For use only by or under the supervision of a licensed practitioner who is experienced in the use and administration of Nitrogen and is familiar with the indications, effects, dosages, methods, and frequency and duration of administration, and with the hazards, contraindications, and side effects, and the precautions to be taken. WARNING: CONTAINS GAS UNDER PRESSURE; MAY EXPLODE IF HEATED. MAY DISPLACE OXYGEN AND CAUSE RAPID SUFFOCATION. Do not handle until all safety precautions have been read and understood. Use and store only outdoors or in a well-ventilated place. Use a back flow preventive device in the piping. Use only with equipment rated for cylinder pressure. Close valve after each use and when empty. Protect from sunlight when ambient temperature exceeds 52 degrees C (125 degrees F). Read and follow the Safety Data Sheet (SDS) before use. FIRST AID: IF INHALED: Remove person to fresh air and keep comfortable for breathing. Get medical advice/attention. CAS: 7727-37-9
DO NOT REMOVE THIS PRODUCT LABEL